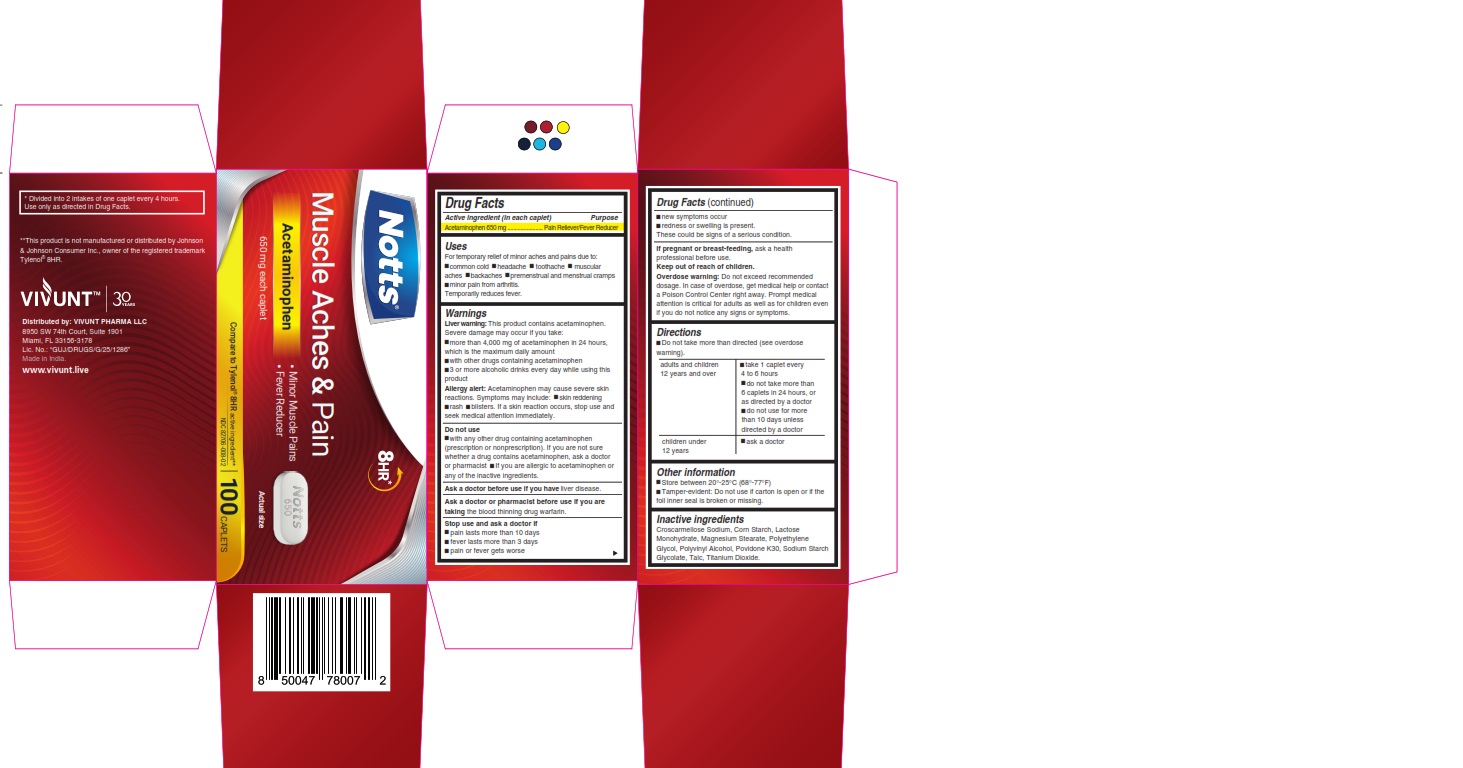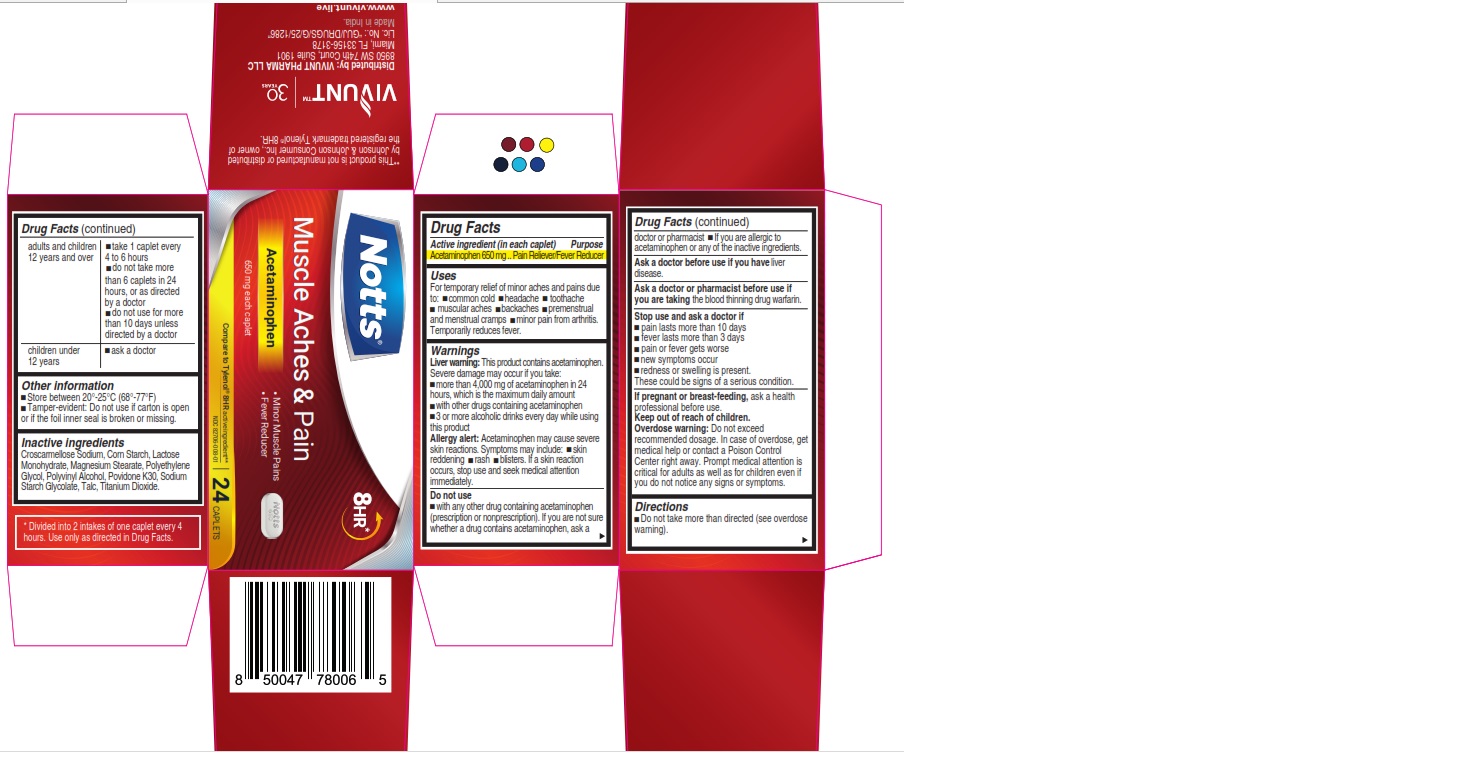 DRUG LABEL: NOTTS - Muscle Aches and Pain
NDC: 82706-008 | Form: TABLET
Manufacturer: VIVUNT PHARMA LLC
Category: otc | Type: HUMAN OTC DRUG LABEL
Date: 20241217

ACTIVE INGREDIENTS: ACETAMINOPHEN 650 mg/1 1
INACTIVE INGREDIENTS: POLYETHYLENE GLYCOL, UNSPECIFIED; TALC; MAGNESIUM STEARATE; MICROCRYSTALLINE CELLULOSE; LECITHIN, SOYBEAN; TITANIUM DIOXIDE; POLYVINYL ALCOHOL, UNSPECIFIED; STEARIC ACID; SODIUM STARCH GLYCOLATE TYPE A; POVIDONE; STARCH, CORN

NOTTS - Muscle Aches & Pain

Drug Facts

ACTIVE INGREDIENT

Active ingredient (in each caplet) | Purpose
Acetaminophen 650 mg | Pain Reliever/Fever Reducer

Uses

For temporary relief of minor aches and pains due to:

● common cold
● headache
● toothache
● muscular aches
● backaches
● premenstrual and menstrual cramps
● minor pain from arthritis

Temporarily reduces fever

Warnings

Liver Warning

This product contains acetaminophen. Severe damage may occur if you take:

● more than 4,000 mg of acetaminophen in 24 hours, which isthe maximum daily amount.
● with other drugs containing acetaminophen
● 3 or more alcoholic drinks every day while using this product

Allergy Alert

Acetaminophen may cause severe skin reactions. Symptoms may include:

- skin reddening
- rash
- blisters

If a skin reaction occurs, stop use and seek medical attention immediately.

Do not use

- with any other drug containing acetaminophen (prescription or nonprescription). If you are not sure whether a drug contains acetaminophen, ask a doctor or pharmacist.
- if you are allergic to acetaminophen or any of the inactive ingredients.

Ask a doctor before use if you have

- liver disease

Ask a doctor or pharmacist before use if you are taking

the blood thinning drug warfarin

Stop use and ask a doctor if

- pain lasts more than 10 days
- pain lasts more than 3 days
- pain or fever gets worse
- new symptoms occur
- redness or swelling is present

These could be signs of a serious condition.

If pregnant or breast-feeding,

ask a health professional before use

Keep out of reach of children.

Overdose warning

Do not exceed recommended dosage. In case of overdose, get medical help or contact a Poison Control Center right away. Prompt medical attention is critical for adults as well as for children even if you do not notice any signs or symptoms.

Directions

- Do not take more than directed (see overdose warning)

adults and children 12 years and over | - take 1 caplets every 4 to 6 hours - do not take more than 6 caplets in 24 hours, or as directed by a doctor - do not use for more than 10 days unless directed by a doctor
children under 12 years | ask a doctor

Other information

- Store between 20-25°C (68-77°F)
- Tamper-evident: Do not use if carton is open or if the foil inner seal is broken or missing.

Inactive ingredients

Croscarmellose Sodium, Corn Starch, Lactose Monohydrate, Magnesium Stearate, Polyethylene Glycol, Polyvinyl Alcohol, Povidone K30, Sodium Starch Glycolate, Talc, Titanium Dioxide.

* Divided into 2 intakes of one caplet every 4 hours. Use only as directed in Drug Facts.

**This product is not manufactured or distributed by Johnson & Johnson Consumer Inc., owner of the registered trademark Tylenol® 8HR.

Distributed by:

VIVUNT PHARMA LLC

8950 SW 74th Court, Suite 1901

Miami, Florida FL 33156-3178

Made in India

PRINCIPAL DISPLAY PANEL - 24 Caplets

NOTTS™ 8HR*

Muscle Aches & Pain

Acetaminophen

- Minor Muscle Aches
- Fever Reducer

Compare to Tylenol® 8HR active ingredients**

NDC 82706-008-01

650 mg each caplet

24 CAPLETS

PRINCIPAL DISPLAY PANEL - 100 Caplets

NOTTS™ 8HR*

Muscle Aches & Pain

Acetaminophen

- Minor Muscle Aches
- Fever Reducer

Compare to Tylenol® 8HR active ingredients**

NDC 82706-008-02

650 mg each caplet

100 CAPLETS